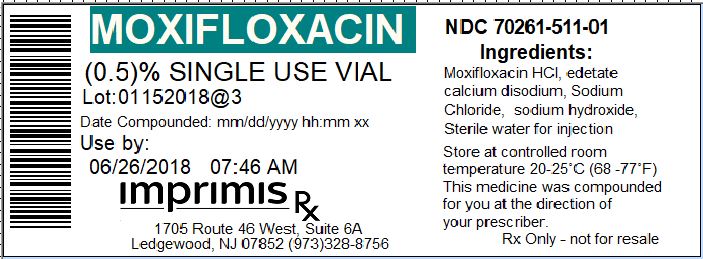 DRUG LABEL: Moxifloxacin PF
NDC: 70261-511 | Form: INJECTION, SOLUTION
Manufacturer: ImprimisRx NJ
Category: prescription | Type: HUMAN PRESCRIPTION DRUG LABEL
Date: 20180508

ACTIVE INGREDIENTS: MOXIFLOXACIN HYDROCHLORIDE MONOHYDRATE 5 mg/1 mL
INACTIVE INGREDIENTS: SODIUM CHLORIDE 8 mg/1 mL

STORAGE AND HANDLING

Store at 20° to 25° C (68° to 77° F)